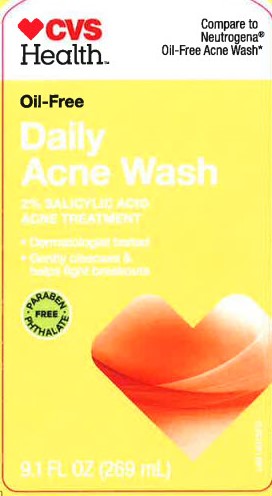 DRUG LABEL: Oil Free Acne Wash
NDC: 59779-961 | Form: LOTION
Manufacturer: CVS Pharmacy, Inc.
Category: otc | Type: HUMAN OTC DRUG LABEL
Date: 20260203

ACTIVE INGREDIENTS: SALICYLIC ACID 20 mg/1 mL
INACTIVE INGREDIENTS: WATER; SODIUM C14-16 OLEFIN SULFONATE; COCAMIDOPROPYL BETAINE; GLYCERIN; SODIUM CHLORIDE; DECYL GLUCOSIDE; EDETATE DISODIUM ANHYDROUS; LINOLEAMIDOPROPYL PG-DIMONIUM CHLORIDE PHOSPHATE; PROPYLENE GLYCOL; ALOE VERA LEAF; CHAMAEMELUM NOBILE FLOWER; CHAMOMILE; FD&C YELLOW NO. 5; FD&C RED NO. 40

CVS 947.003/947AC-AD
Oil Free Acne Wash

Active ingredient

Salicylic acid 2%

Purpose

Acne medication

Use

for the treatment of acne

Warnings

For external use only

When using this product

- skin irritation and dryness is more likely to occur if you use another topical acne medication at the same time. If irritation occurs, only use one topical acne medication at a time.

Keep out of reach of children.

If swallowed, get medical help or contact a Poison Control Center right away.

Directions

- use up to twice a daily. Wet face, apply to hands, add water and work into lather. Massage face gently. Rinse well.
- avoid contact with eyes. If contact occurs, flush thoroughly with water.

Inactive ingredients

water, sodium C14-16 olefin sulfonate, cocamidopropyl betaine, glycerin, sodium chloride, decyl glucoside, disodium EDTA, fragrance, linoleamidopropyl PG-dimonium chloride phosphate, propylene glycol, Aloe barbadensis leaf extract, Anthemis nobilis flower extract, Chamomilla recutita (matricaria) flower extract, yellow 5, red 40

*This product is not manufactured or distributed by NEUTROGENA CORPORATION, distributor of Neutrogena Oil-Free Acne Wash.

Distributed by: CVS Pharmacy, Inc.

One CVS Drive, Woonsocket, RI 02895

(c) 2018 CVS/pharmacy

CVS.com

1-800-SHOP CVS

Made in the USA with US and foreign parts

principal display panel

CVS Health

Compare to Neutrogena Oil-Free Acne Wash*

Oil-Free

Daily

Acne Wash

2% SALICYLIC ACID ACNE TREATMENT

Dermatologist tested
Gently cleanses & helps fight breakouts
9.1 FL OZ (269 mL)